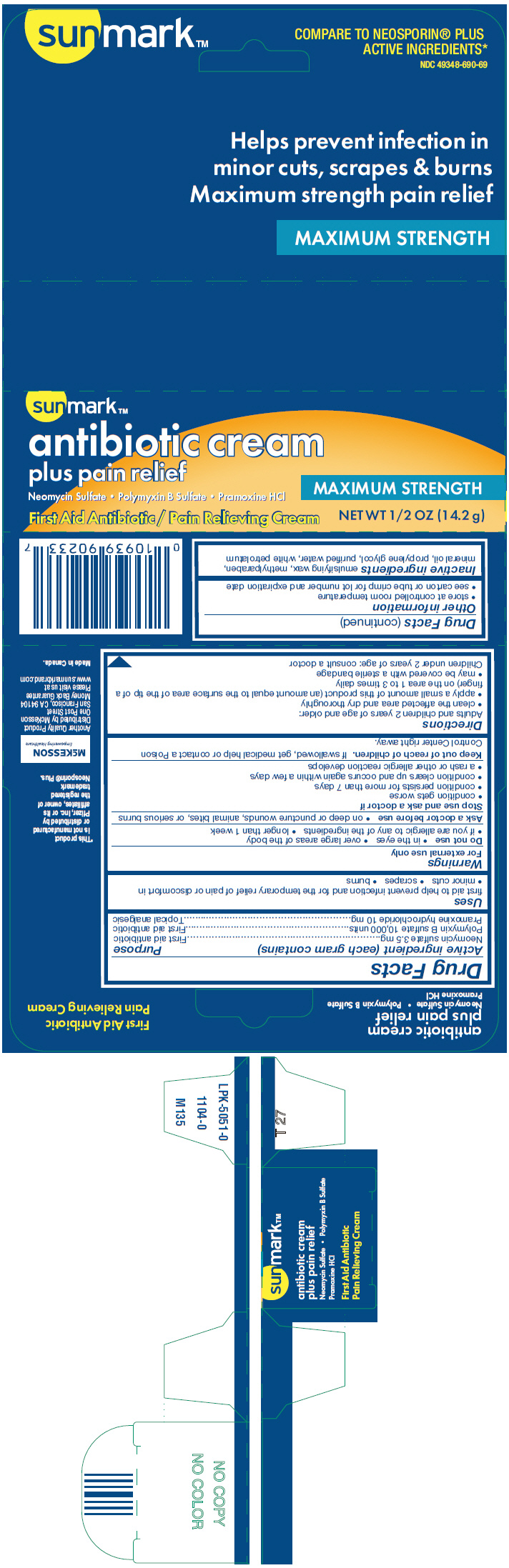 DRUG LABEL: sunmark

NDC: 49348-690 | Form: CREAM
Manufacturer: Strategic Sourcing Services LLC
Category: otc | Type: HUMAN OTC DRUG LABEL
Date: 20250716

ACTIVE INGREDIENTS: NEOMYCIN SULFATE 3.5 mg/1 g; POLYMYXIN B SULFATE 10000 [iU]/1 g; PRAMOXINE HYDROCHLORIDE 10 mg/1 g
INACTIVE INGREDIENTS: METHYLPARABEN; MINERAL OIL; PROPYLENE GLYCOL; WATER; PETROLATUM

sunmark™
antibiotic plus pain relief

Drug Facts

ACTIVE INGREDIENT

Active ingredient (each gram contains) | Purpose
Neomycin sulfate 3.5 mg | First aid antibiotic
Polymyxin B sulfate 10,000 units | First aid antibiotic
Pramoxine hydrochloride 10 mg | Topical analgesic

Uses

first aid to help prevent infection and for the temporary relief of pain or discomfort in

- minor cuts
- scrapes
- burns

Warnings

For external use only

Do not use

- in the eyes
- over large areas of the body
- if you are allergic to any of the ingredients
- longer than 1 week

Ask a doctor before use

- on deep or puncture wounds, animal bites, or serious burns

Stop use and ask a doctor if

- condition gets worse
- condition persists for more than 7 days
- condition clears up and occurs again within a few days
- a rash or other allergic reaction develops

Keep out of reach of children.If swallowed, get medical help or contact a Poison Control Center right away.

Directions

Adults and children 2 years of age and older:

- clean the affected area and dry thoroughly
- apply a small amount of this product (an amount equal to the surface area of the tip of a finger) on the area 1 to 3 times daily
- may be covered with a sterile bandage

Children under 2 years of age: consult a doctor

Other information

- store at controlled room temperature
- see carton or tube crimp for lot number and expiration date

Inactive ingredients

emulsifying wax, methylparaben, mineral oil, propylene glycol, purified water, white petrolatum

Distributed by McKesson
One Post Street
San Francisco, CA 94104

PRINCIPAL DISPLAY PANEL - 14.2 g Tube Carton

sunmark™

antibiotic cream
plus pain relief

Neomycin Sulfate • Polymyxin B Sulfate • Pramoxine HCl

MAXIMUM STRENGTH

First Aid Antibiotic / Pain Relieving Cream

NET WT 1/2 OZ (14.2 g)